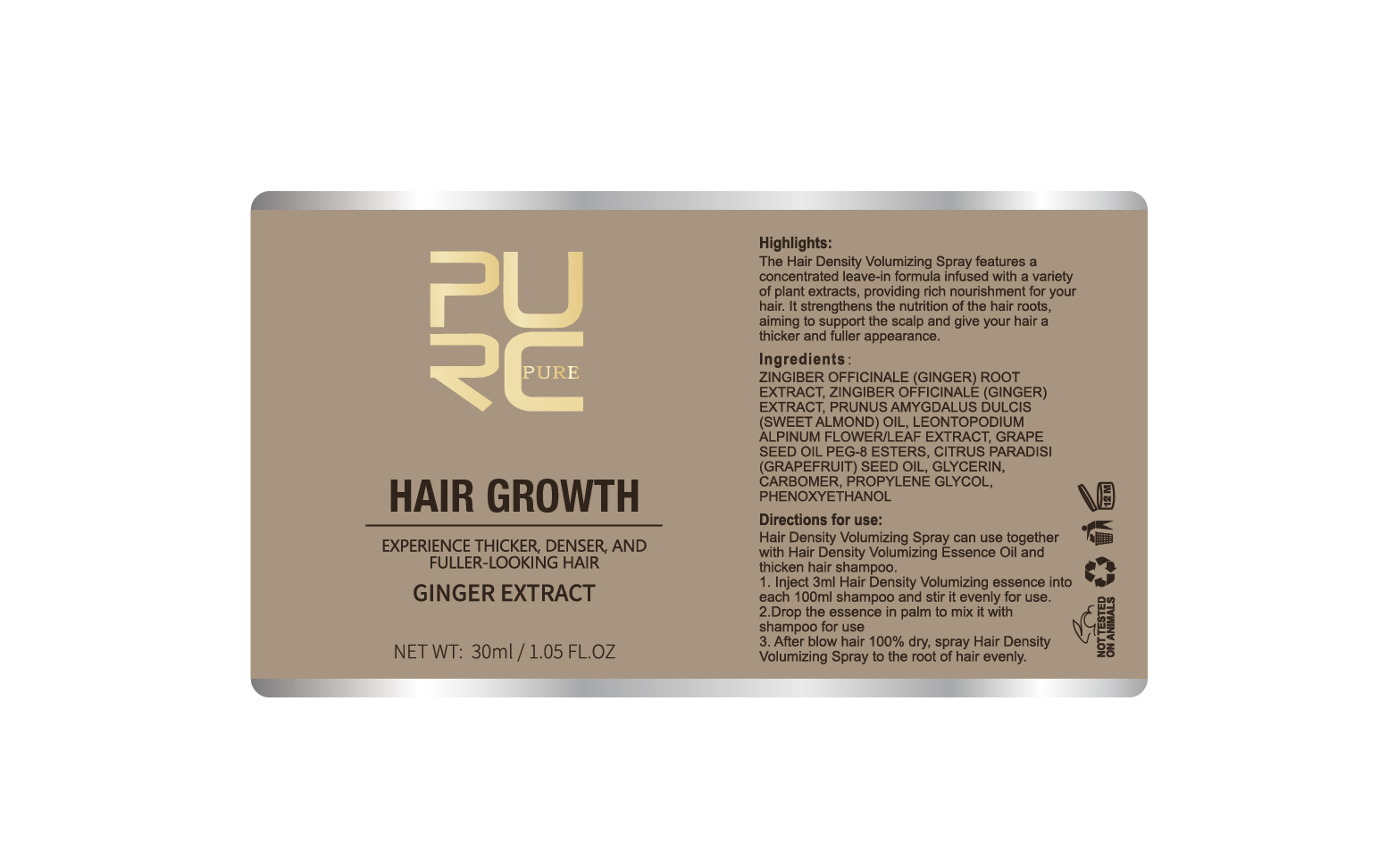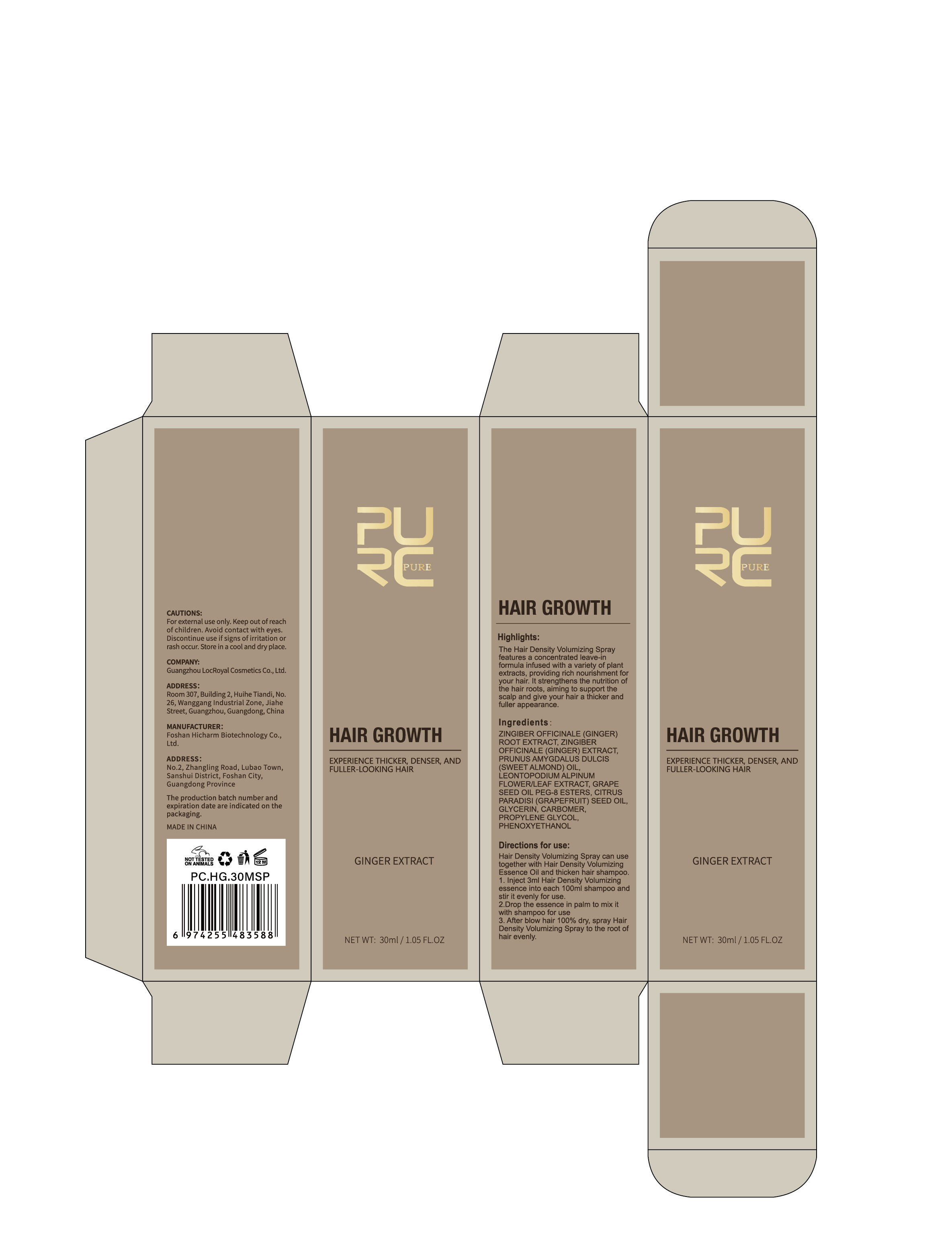 DRUG LABEL: PURC  HAIR GROWTH
NDC: 84186-016 | Form: SPRAY
Manufacturer: Guangzhou Bonnieco Cosmetics Co., Ltd
Category: otc | Type: HUMAN OTC DRUG LABEL
Date: 20240429

ACTIVE INGREDIENTS: GINGER 4 g/100 mL
INACTIVE INGREDIENTS: LEONTOPODIUM ALPINUM FLOWERING TOP; ZINGIBER OFFICINALE WHOLE; GRAPEFRUIT SEED OIL; GLYCERIN; PROPYLENE GLYCOL; PHENOXYETHANOL; CARBOXYPOLYMETHYLENE; CANOLA OIL; ALMOND OIL

84186-016

Active Ingredient

ZINGIBER OFFICINALE (GINGER) ROOT EXTRACT 4%

Purpose

hair (on the head)

Use

Hair Density Volumizing Spray can usetogether with Hair Density VolumizingEssence Oil and thicken hair shampoo.1.Inject 3ml Hair Density Volumizingessence into each 100ml shampoo andstir it evenly for use.2.Drop the essence in palm to mix itwith shampoo for use 3.After blow hair 100% dry, spray HairDensity Volumizing Spray to the root ofhair evenly.

Warnings

For external use only. Keep out of reachof children.Avoid contact with eyes.Discontinue use if signs of irritation orrash occur. Store in a cool and dry place.

Do not use

The Hair Density Volumizing Sprayfeatures a concentrated leave-in formula infused with a variety of plantextracts, providing rich nourishment foryour hair. It strengthens the nutrition ofthe hair roots, aiming to support thescalp and give your hair a thicker andfuller appearance.

When Using

In case of contact with the eyes, rinse immediately with plenty of water.

Stop Use

If discomfort arises, please immediately stop using the product and seek the assistance of a dermatologist.

Ask Doctor

If discomfort arises, please immediately stop using the product and seek the assistance of a dermatologist.

Keep Oot Of Reach Of Children, If a child accidentally swallows it, please call the emergency center immediately.

Directions

Hair Density Volumizing Spray can usetogether with Hair Density VolumizingEssence Oil and thicken hair shampoo.1.Inject 3ml Hair Density Volumizingessence into each 100ml shampoo andstir it evenly for use.2.Drop the essence in palm to mix itwith shampoo for use 3.After blow hair 100% dry, spray HairDensity Volumizing Spray to the root ofhair evenly.

Inactive ingredients

PRUNUS AMYGDALUS DULCIS (SWEET ALMOND) OIL, ZINGIBER OFFICINALE (GINGER) ROOT EXTRACT, LEONTOPODIUM ALPINUM FLOWER/LEAF EXTRACT, GRAPE SEED OIL PEG-8 ESTERS, CITRUS PARADISI (GRAPEFRUIT) SEED OIL, GLYCERIN, CARBOMER, PROPYLENE GLYCOL, PHENOXYETHANOL, ZINGIBER OFFICINALE (GINGER) EXTRACT